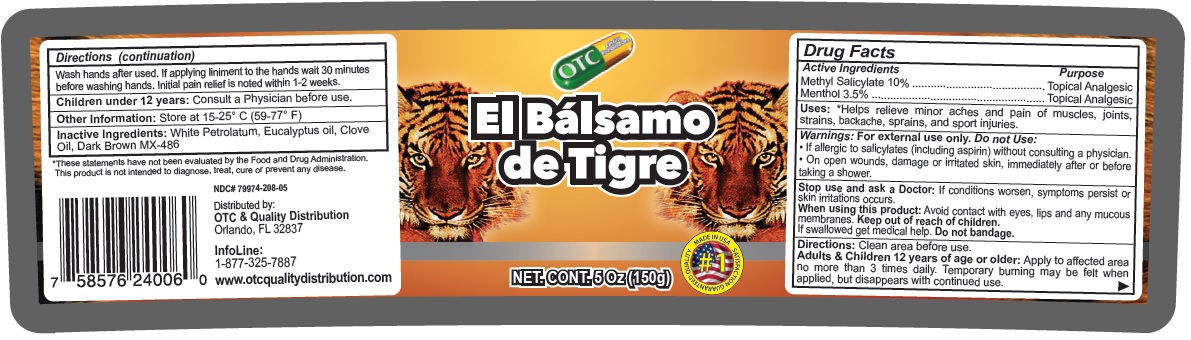 DRUG LABEL: El Balsamo de Tigre
NDC: 79974-208 | Form: OINTMENT
Manufacturer: Miramar Cosmetics, Inc DBA Miramar Lab
Category: otc | Type: HUMAN OTC DRUG LABEL
Date: 20250113

ACTIVE INGREDIENTS: METHYL SALICYLATE 10 g/100 g; MENTHOL, UNSPECIFIED FORM 3.5 g/100 g
INACTIVE INGREDIENTS: WHITE PETROLATUM; EUCALYPTUS OIL; CLOVE OIL; D&C GREEN NO. 6; D&C RED NO. 17; D&C YELLOW NO. 11

El Bálsamo de Tigre

Active Ingredients

Methyl Salicylate 10%
Menthol 3.5%

Purpose

Topical Analgesic

Uses:

*Helps relieve minor aches and pain of muscles, joints, strains, backache, sprains, and sport injuries.

Warnings:

For external use only.

Do not Use:
• If allergic to salicylates (including aspirin) without consulting a physician.
• On open wounds, damage or irritated skin, immediately after or before taking a shower.

Stop use and ask a Doctor: If conditions worsen, symptoms persist or skin irritations occurs.

When using this product: Avoid contact with eyes, lips and any mucous membranes.

Keep out of reach of children.
If swallowed get medical help. Do not bandage.

Directions:

Clean area before use.
Adults & Children 12 years of age or older: Apply to affected area no more than 3 times daily. Temporary burning may be felt when applied, but disappears with continued use.
Wash hands after used. If applying liniment to the hands wait 30 minutes before washing hands. Initial pain relief is noted within 1-2 weeks.

Children under 12 years: Consult a Physician before use.

Other Information:

Store at 15-25° C (59-77° F)

Inactive Ingredients:

White Petrolatum, Eucalyptus oil, Clove Oil, Dark Brown MX-486

MADE IN USA
SATISFACTION GUARANTEED QUALITY

*These statements have not been evaluated by the Food and Drug Administration.
This product is not intended to diagnose, treat, cure or prevent any disease.

Distributed by:
OTC & Quality Distribution
Orlando, FL 32837

InfoLine:
1-877-325-7887

www.otcqualitydistribution.com